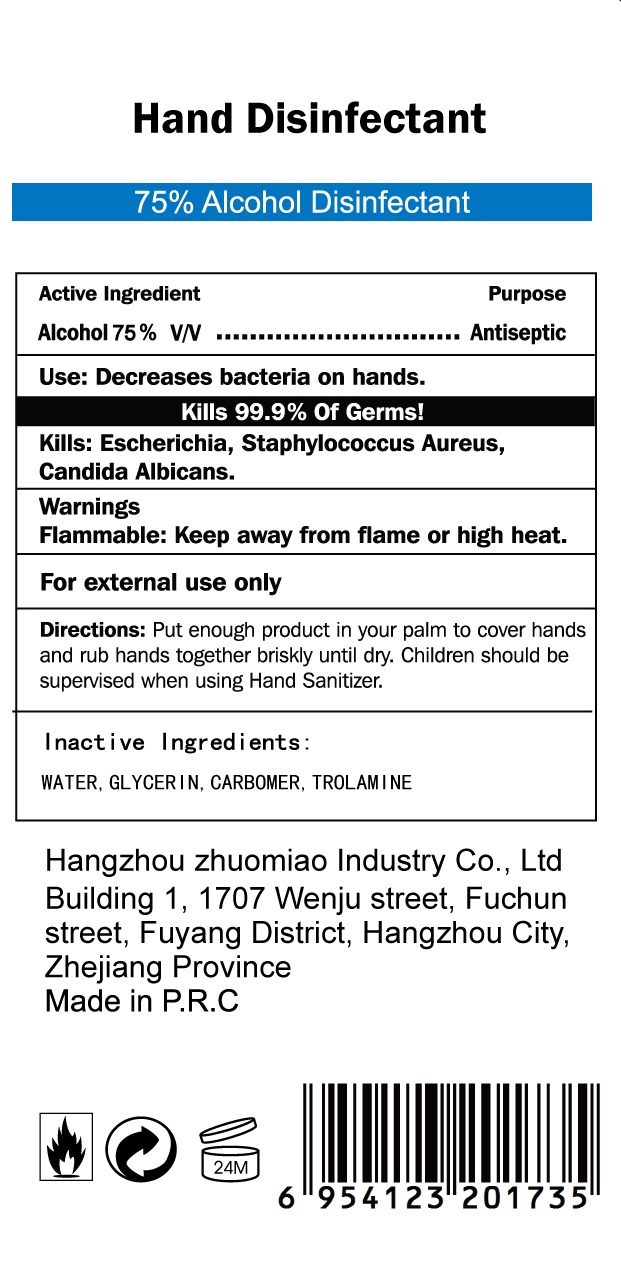 DRUG LABEL: Hand Sanitizer
NDC: 76954-002 | Form: GEL
Manufacturer: Hangzhou zhuomiao Industry Co., Ltd.
Category: otc | Type: HUMAN OTC DRUG LABEL
Date: 20200523

ACTIVE INGREDIENTS: ALCOHOL 75 mL/100 mL
INACTIVE INGREDIENTS: WATER; TROLAMINE; GLYCERIN; CARBOMER INTERPOLYMER TYPE B (ALLYL PENTAERYTHRITOL CROSSLINKED)

DOSAGE AND ADMINISTRATION

For external use only.

INACTIVE INGREDIENT

WATER, GLYCERIN, CARBOMER, TROLAMINE

INDICATIONS AND USAGE

Put enough product in your palm to cover hands and rub hands together briskly until dry.

Children should be supervised when using Hand Sanitizer

PURPOSE

Decrease bacteria on hands.

ACTIVE INGREDIENT

Alcohol 75% v/v................Antiseptic

WARNINGS

Flammable: Keep away from flame or high heat.